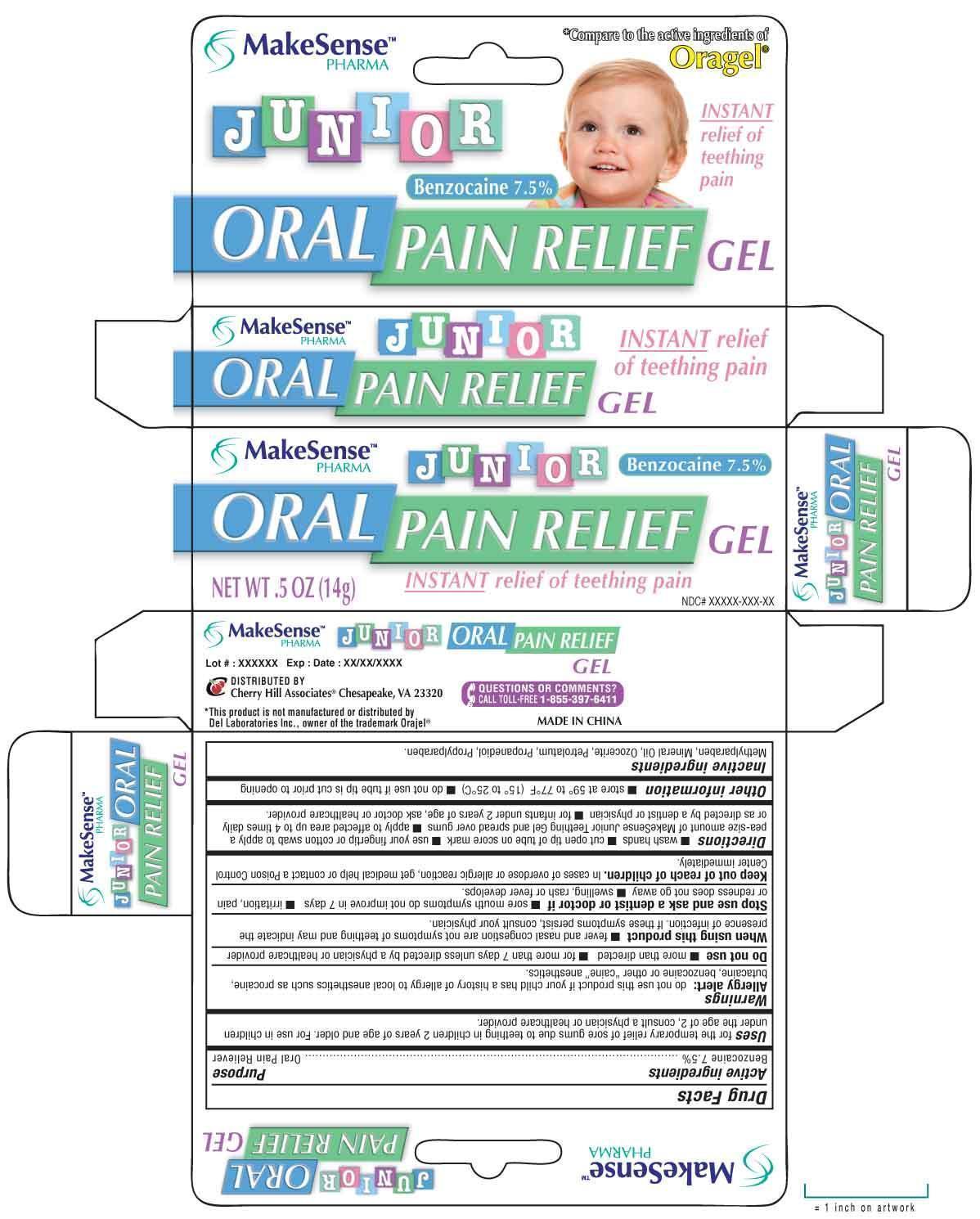 DRUG LABEL: MAKESENSE
NDC: 69020-206 | Form: GEL
Manufacturer: Cherry Hill Sales Co
Category: otc | Type: HUMAN OTC DRUG LABEL
Date: 20140730

ACTIVE INGREDIENTS: BENZOCAINE 7.5 g/100 g
INACTIVE INGREDIENTS: METHYLPARABEN; MINERAL OIL; CERESIN; PETROLATUM; PROPANEDIOL; PROPYLPARABEN

Drug Facts

Active Ingredient

Benzocaine 7.5%

Purpose

Oral Pain Reliever

Uses

for the temporary relief of sore gums due to teething in children 2 years of age and older. For use in children under the age of 2, consult a physician or healthcare provider.

Warnings

Allergy alert: do not use this product if your baby has a history of allergy to local anesthetics such as procaine, butacaine or other "caine" anesthetics

Do not use

■ more than directed ■ for more than 7 days unless directed by a physician or healthcare provider

When using this product

■ fever and nasal congestion are not symptoms of teething and may indicate the presence of infection. If these symptoms persist, consult your physician

Stop use and ask a dentist or doctor if

■ sore mouth symptoms do not get better in 7 days ■ irritation, pain or redness does not go away ■ swelling, rash or fever develops

Keep out of reach of children

In case of overdose or allergic reaction get medical help or contact a Poison Control Center immediately.

Directions

■ wash hands ■ cut open tip of tube on score mark ■ use your fingertip or cotton applicator to apply a small pea-size amount of MakeSense Junior Teething Gel and spread over gums ■ apply to affected area up to 4 times daily or as directed by a dentist or physician ■ for infants under 2 years of age, ask a doctor or health care provider

Other information

■ store at 59 to 77F (15-25C) ■ do not use if tube tip is cut prior to opening

Inactive ingredients

Methylparaben, Mineral Oil, Ozocerite, Petrolatum, Propanediol, Propylparaben